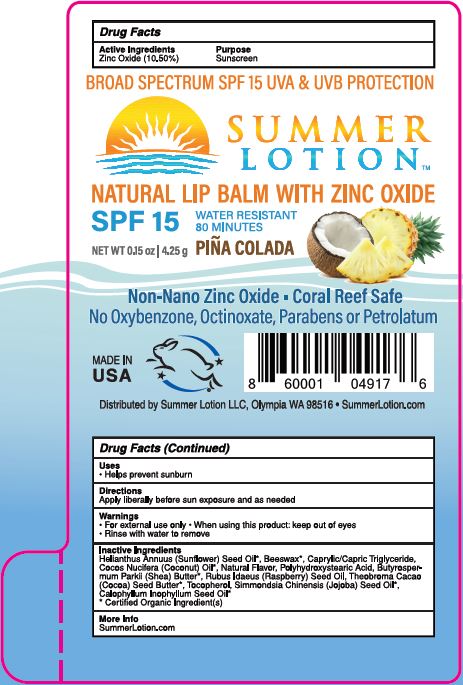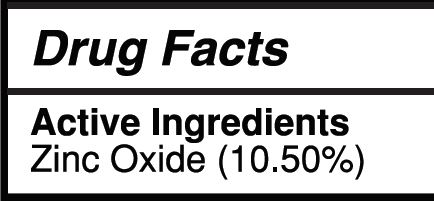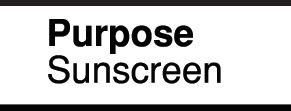 DRUG LABEL: Zinc Oxide Lip Balm Pina Colada
NDC: 62932-245 | Form: STICK
Manufacturer: Private Label Select Ltd CO
Category: otc | Type: HUMAN OTC DRUG LABEL
Date: 20201231

ACTIVE INGREDIENTS: ZINC OXIDE 10 g/100 g
INACTIVE INGREDIENTS: .BETA.-TOCOPHEROL; .GAMMA.-TOCOPHEROL; JOJOBA OIL; POLYHYDROXYSTEARIC ACID (2300 MW); COCOA BUTTER; COCONUT OIL; SHEA BUTTER; RASPBERRY SEED OIL; SUNFLOWER OIL; POLYHYDROXYSTEARIC ACID STEARATE; MEDIUM-CHAIN TRIGLYCERIDES; .ALPHA.-TOCOPHEROL, D-; .DELTA.-TOCOPHEROL; TAMANU OIL; WHITE WAX

Summer Lotion SPF 15 Lip Balm Pina Colada